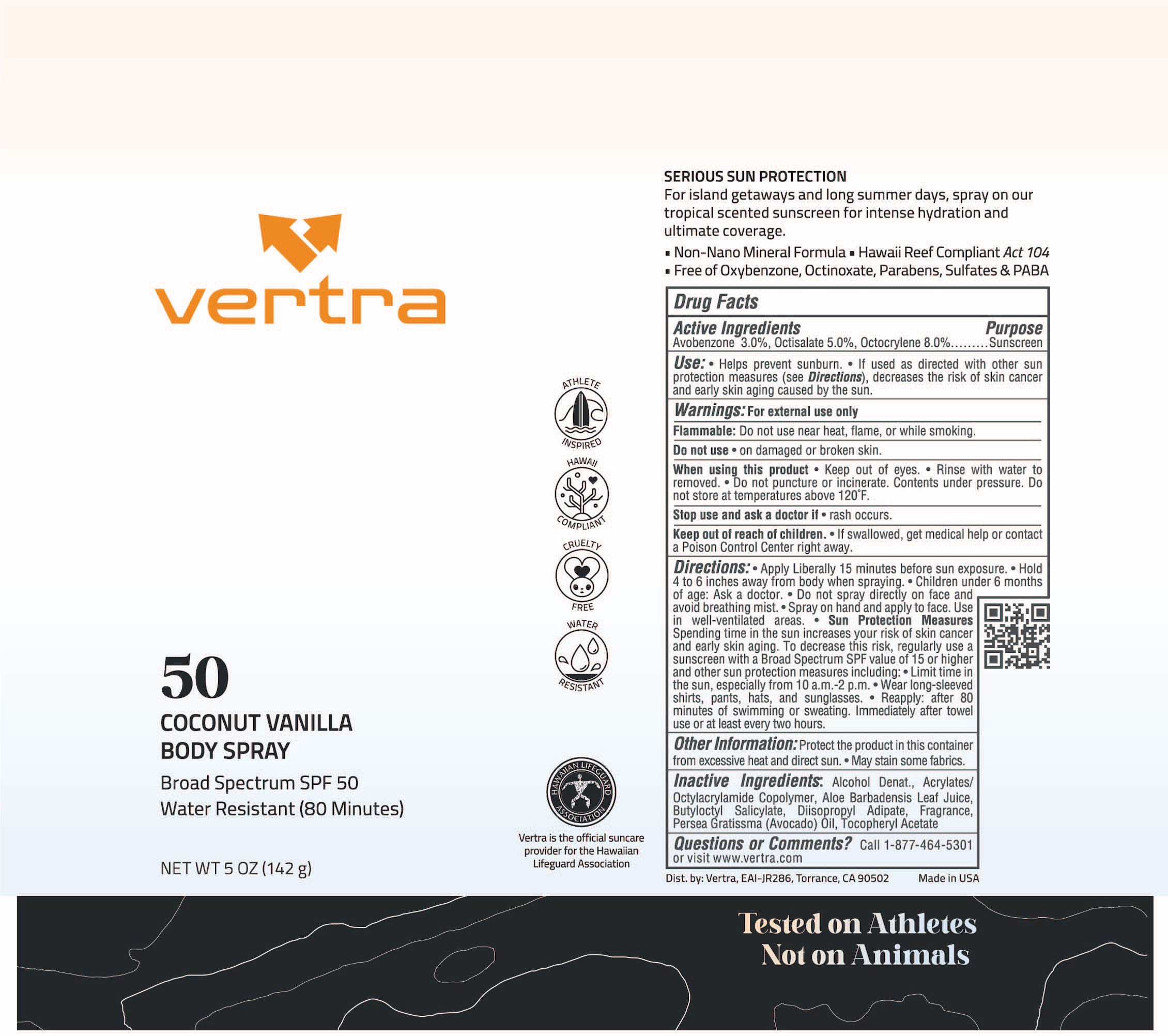 DRUG LABEL: Coconut Vanilla Body Broad Spectrum SPF 50
NDC: 71014-094 | Form: SPRAY
Manufacturer: EAI-JR286, Inc
Category: otc | Type: HUMAN OTC DRUG LABEL
Date: 20251007

ACTIVE INGREDIENTS: OCTISALATE 5 g/100 g; AVOBENZONE 3 g/100 g; OCTOCRYLENE 8 g/100 g
INACTIVE INGREDIENTS: ALCOHOL; ALOE VERA LEAF; DIISOPROPYL ADIPATE; .ALPHA.-TOCOPHEROL ACETATE; AVOCADO OIL; BUTYLOCTYL SALICYLATE

Coconut Vanilla Body Spray Broad Spectrum SPF 50

Active ingredients Purpose

Avobenzone 3.0, Octisalate 5.0% Octocrylene 8.0% Sunscreen

Uses

- Helps prevent sunburn
- If used as directed with other sun protection measures (see D irections) decreases the risk of skin cancer and early skin aging caused by the sun

Keep out of reach of children.

- If swallowed, get medical help or contact a Poison Control Center right away

Stop use and ask a doctor if

- rash occurs

WARNINGS

For external use only

Flammable: Do not use near heat, flame, or while smoking

Do not use

- on damaged or broken skin

When using this product

- Keep out of eyes
- Rinse with water to remove
- Do not puncture or incinerate. Contents under pressure. Do not store at temperatures above 120ºF.

Directions:

- Apply Liberally 15 minutes before sun exposure
- Hold 4 to 6 inches away from body when spraying
- Children under 6 months of age: Ask a doctor
- Do not spray directly on face and avoid breathing mist
- Spray on hand and and apply to face. Use in a well-ventillated area

Sun Protection Measures:

Spending time in the sun increases your risk of skin cancer and early skin aging. To decrease this risk, regularly use a sunscreen with a broad spectrum SPF value of 15 or higher and other sun protection measures including:

Limit time in the sun, especially from 10 a.m.- 2p.m.

Wear long sleeved shirts, pants, hats and sunglasses

Reapply: After 80 minutes of swimming. Immediately after towel use or at least every 2 hours

INACTIVE INGREDIENT

Inactive ingredients: Alcohol Denat., Acrylates/ Octylacrylamide Copolymer, Aloe Barbadensis Leaf Juice, Butyloctyl Salicylate, Diisopropyl Adipate, Fragrance, Persea Gratissima (Avocado) Oil, Tocopheryl Acetate

OTHER SAFETY INFORMATION

Protect the product in this container from excessive heat and direct sun

May stain some fabrics

PACKAGE LABEL

vertra

50

Coconut Vanilla Body Spray

Broad Spectrum SPF 50

Water Resistant (80 Minutes)

NET WT 5 OZ (142 g)